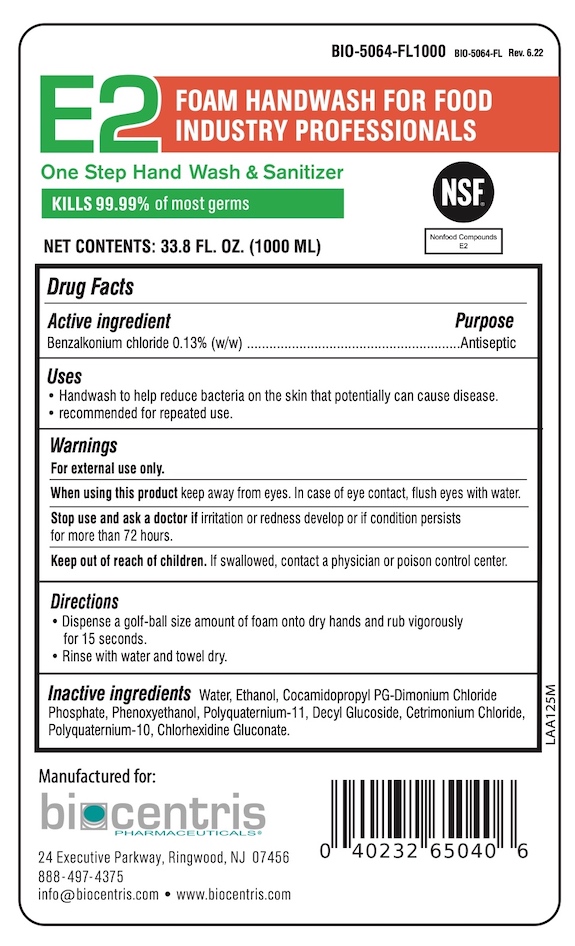 DRUG LABEL: Biocentris E2 Handwash
NDC: 81232-402 | Form: LIQUID
Manufacturer: Biocentris Pharmaceuticals, LLC
Category: otc | Type: HUMAN OTC DRUG LABEL
Date: 20220630

ACTIVE INGREDIENTS: BENZALKONIUM CHLORIDE 0.13 g/100 mL
INACTIVE INGREDIENTS: CETRIMONIUM CHLORIDE; CHLORHEXIDINE GLUCONATE; COCAMIDOPROPYL PG-DIMONIUM CHLORIDE PHOSPHATE; DECYL GLUCOSIDE; ALCOHOL; PHENOXYETHANOL; POLYQUATERNIUM-10 (1000 MPA.S AT 2%); POLYQUATERNIUM-11 (1000000 MW); WATER

Biocentris E2 Foam Handwash

Drug Facts

Active ingredient

Benzalkonium chloride 0.13% w/w

Purpose

Antiseptic

Uses

- Handwash to help reduce bacteria on the skin that potentially can cause disease.
- Recommended for repeated use.

Warnings

For external use only.

When using this product keep away from eyes. In case of eye contact, flush eyes with water.

Stop use and ask a doctor if irritation and redness develop or if condition persists for more than 72 hours.

Keep out of reach of children. If swallowed, contact a physician or poison control center.

Directions

- Dispense a golf ball size amount of foam onto dry hands and rub vigorously for 15 seconds
- Rinse with water and towel dry.

INACTIVE INGREDIENT

Inactive ingredients Water, Ethanol, Cocamidopropyl PG-Dimonium Chloride Phosphate, Phenoxyethanol, Polyquatemium 11, Decyl Glucoside, Cetrimonium Chloride, Polyquatemium-10, Chlorhexidine Gluconate

Manufactured for:

biocentris PHARMACEUTICALS

24 Executive Parkway, Ringwood, NJ 07456

888-497-4375

info@biocentris.com • www.biocentris.com

PACKAGE LABEL

E2 FOAM HANDWASH FOR FOOD INDUSTRY PROFESSIONALS

One Step Hand Wash & Sanitizer

KILLS 99.99% of most germs

NET CONTENTS: 33.8 FL. OZ. (1000 ML)